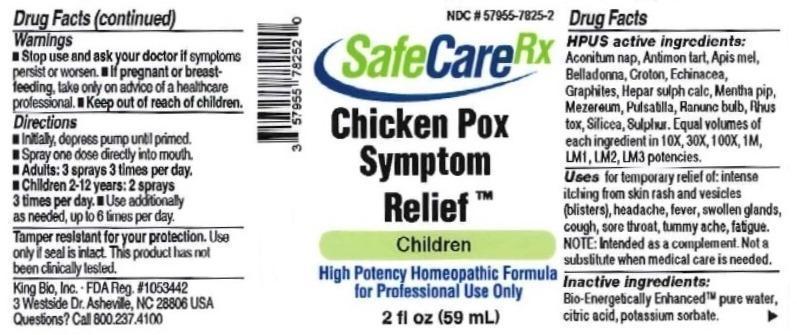 DRUG LABEL: Chicken Pox Symptom Relief
NDC: 57955-7825 | Form: LIQUID
Manufacturer: King Bio Inc.
Category: homeopathic | Type: HUMAN OTC DRUG LABEL
Date: 20160713

ACTIVE INGREDIENTS: ACONITUM NAPELLUS 10 [hp_X]/59 mL; ANTIMONY POTASSIUM TARTRATE 10 [hp_X]/59 mL; APIS MELLIFERA 10 [hp_X]/59 mL; ATROPA BELLADONNA 10 [hp_X]/59 mL; CROTON TIGLIUM SEED 10 [hp_X]/59 mL; ECHINACEA, UNSPECIFIED 10 [hp_X]/59 mL; GRAPHITE 10 [hp_X]/59 mL; CALCIUM SULFIDE 10 [hp_X]/59 mL; MENTHA PIPERITA 10 [hp_X]/59 mL; PULSATILLA VULGARIS 10 [hp_X]/59 mL; RANUNCULUS BULBOSUS 10 [hp_X]/59 mL; TOXICODENDRON PUBESCENS LEAF 10 [hp_X]/59 mL; SILICON DIOXIDE 10 [hp_X]/59 mL; SULFUR 10 [hp_X]/59 mL
INACTIVE INGREDIENTS: WATER; ANHYDROUS CITRIC ACID; POTASSIUM SORBATE

Chicken Pox Symptom Relief™

ACTIVE INGREDIENT

Drug Facts__________________________________________________________________________________________________________

HPUS active ingredients: Aconitum napellus, Antimonium tartaricum, Apis mellifica, Balladonna, Croton tiglium, Echinacea, Graphites, Hepar sulphuris calcareum, Mentha piperita, Mezereum, Pulsatilla, Ranunculus bulbosus, Rhus toxicodendron, Silicea, Sulphur. Equal volumes of each ingredient in 10X, 30X, 100X, 1M, LM1, LM2, LM3 potencies.

INDICATIONS AND USAGE

Uses temporary relief of: intense itching from skin rash and vesicles (blisters), headache, fever, swollen glands, cough, sore throat, tummy ache, fatigue. Note: Intended as a complement. Not a substitute when medical care is needed.

Inactive Ingredients:

Bio-Energetically Enhanced™ pure water, citric acid and potassium sorbate.

Warnings

- Stop use and ask your doctor if symptoms persist or worsen.
- If pregnant or breast-feeding, ask a healthcare professional before ues.

- Keep out of reach of children.

Directions

- Initially, depress pump until primed.
- Spray one dose directly into mouth.
- Ages 12 and up: 3 sprays 3 times per day.
- Children 2-12: 2 sprays 3 times per day.
- Use additionally as needed, up to 6 times per day.

OTHER SAFETY INFORMATION

Tamper resistant for your protection. Use only if safety seal is intact. This product has not been clinically tested.

Note: Intended as a complement. Not a substitute when medical care is needed.

PURPOSE

Uses temporary relief of:

- intense itching from skin rash and vesicles (blisters)
- headache
- fever
- swollen glands
- cough
- sore throat
- tummy ache
- fatigue